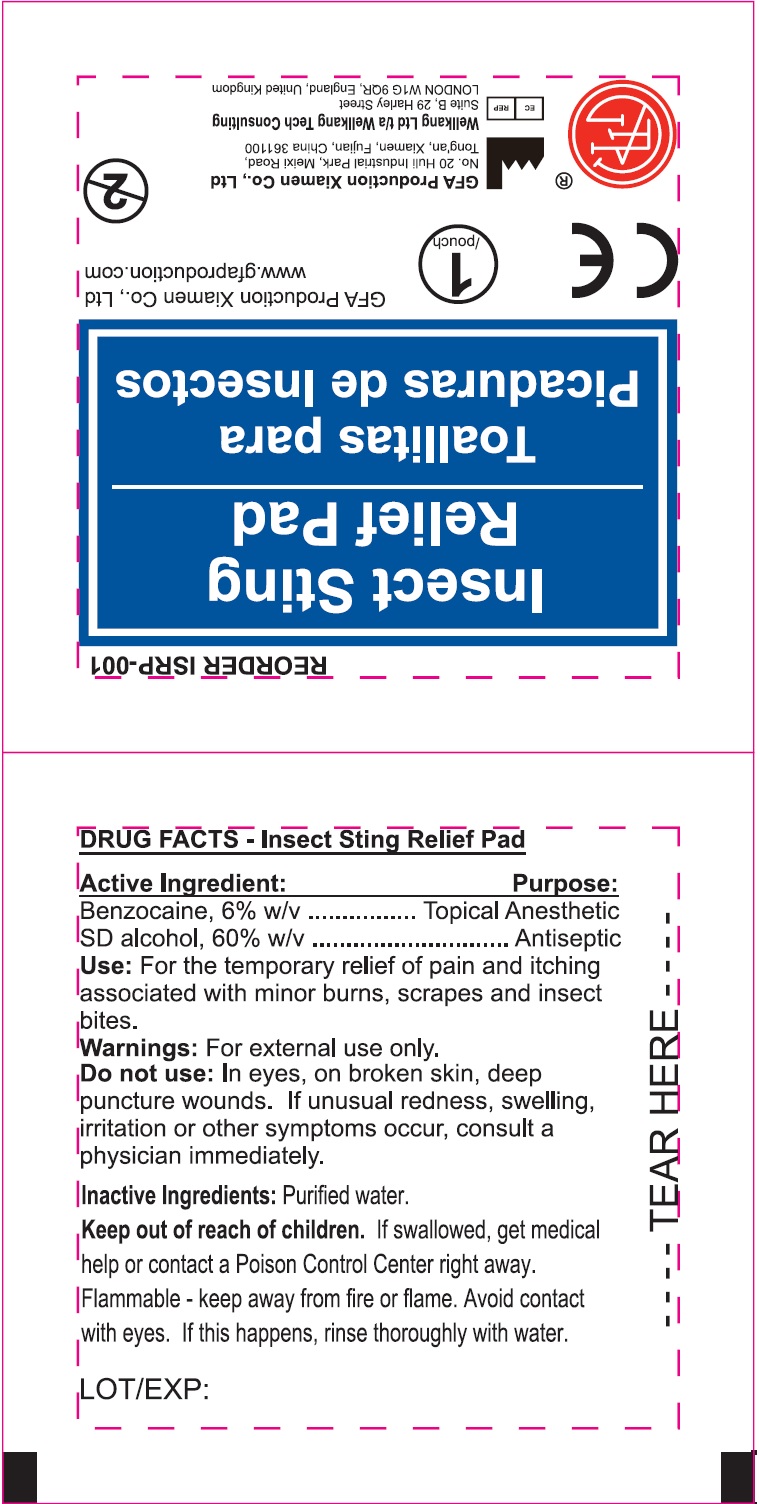 DRUG LABEL: INSECT STING RELIEF
NDC: 50814-038 | Form: SWAB
Manufacturer: GFA Production (Xiamen) Co., Ltd.
Category: otc | Type: HUMAN OTC DRUG LABEL
Date: 20250430

ACTIVE INGREDIENTS: BENZOCAINE 6 g/100 g; ALCOHOL 60 g/100 g
INACTIVE INGREDIENTS: WATER

INSECT STING RELIEF PAD

Active Ingredient:

Benzocaine, 6% w/v

SD alcohol, 60% w/v

Purpose:

Topical Anesthetic

Anesthetic

Use:

For the temporary relief of pain and itching associated with minor burns, scrapes and insect bites.

Warnings:

For external use only.

Do not use:

In eyes, on broken skin, deep puncture wounds. If unsual redness, swelling, irritation or other symptoms occur, consult a physician immediately.

Keep out of reach of children.

If swallowed, get medical help or contact a Poison Contrl Center right away.

Flammable - keep away from fire or flame. Avoid contact with eyes. If this happens, rinse thoroughly with water

Inactive Ingredients:

Purified water.